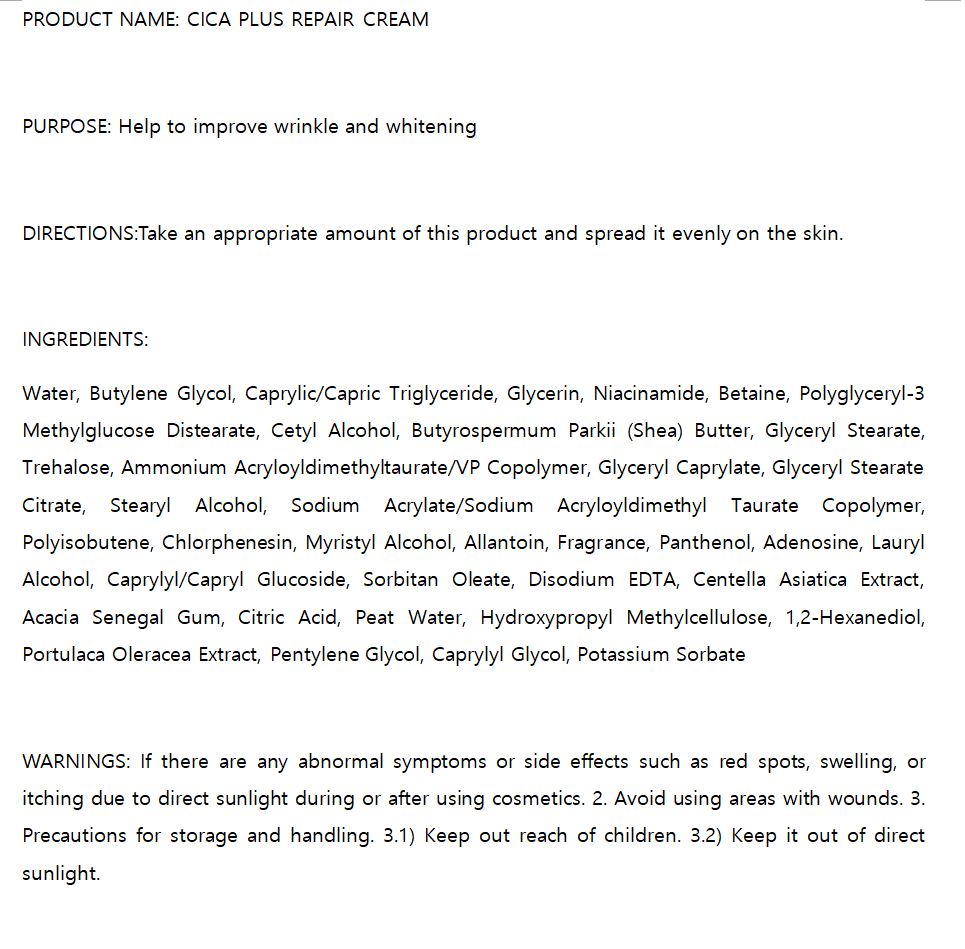 DRUG LABEL: W.SKIN CICA PLUS REPAIR
NDC: 74997-0010 | Form: CREAM
Manufacturer: J&J COMPANY
Category: otc | Type: HUMAN OTC DRUG LABEL
Date: 20210424

ACTIVE INGREDIENTS: NIACINAMIDE 2 g/100 mL; ADENOSINE 0.04 g/100 mL
INACTIVE INGREDIENTS: BUTYLENE GLYCOL; WATER

J&J COMPANY - STOP-AGING PEPTIDE TONER

ACTIVE INGREDIENT

Niacinamide, Adenosine

INACTIVE INGREDIENT

Water, Butylene Glycol, Caprylic/Capric Triglyceride, Glycerin, Niacinamide, Betaine, Polyglyceryl-3 Methylglucose Distearate, Cetyl Alcohol, Butyrospermum Parkii (Shea) Butter, Glyceryl Stearate, Trehalose, Ammonium Acryloyldimethyltaurate/VP Copolymer, Glyceryl Caprylate, Glyceryl Stearate Citrate, Stearyl Alcohol, Sodium Acrylate/Sodium Acryloyldimethyl Taurate Copolymer, Polyisobutene, Chlorphenesin, Myristyl Alcohol, Allantoin, Fragrance, Panthenol, Adenosine, Lauryl Alcohol, Caprylyl/Capryl Glucoside, Sorbitan Oleate, Disodium EDTA, Centella Asiatica Extract, Acacia Senegal Gum, Citric Acid, Peat Water, Hydroxypropyl Methylcellulose, 1,2-Hexanediol, Portulaca Oleracea Extract, Pentylene Glycol, Caprylyl Glycol, Potassium Sorbate

PURPOSE

Help to improve wrinkle and whitening

keep out of reach of the children

INDICATIONS AND USAGE

Take an appropriate amount of this product and spread it evenly on the skin.

WARNINGS

If there are any abnormal symptoms or side effects such as red spots, swelling, or itching due to direct sunlight during or after using cosmetics. 2. Avoid using areas with wounds. 3. Precautions for storage and handling. 3.1) Keep out reach of children. 3.2) Keep it out of direct sunlight.

DOSAGE AND ADMINISTRATION

for external use only